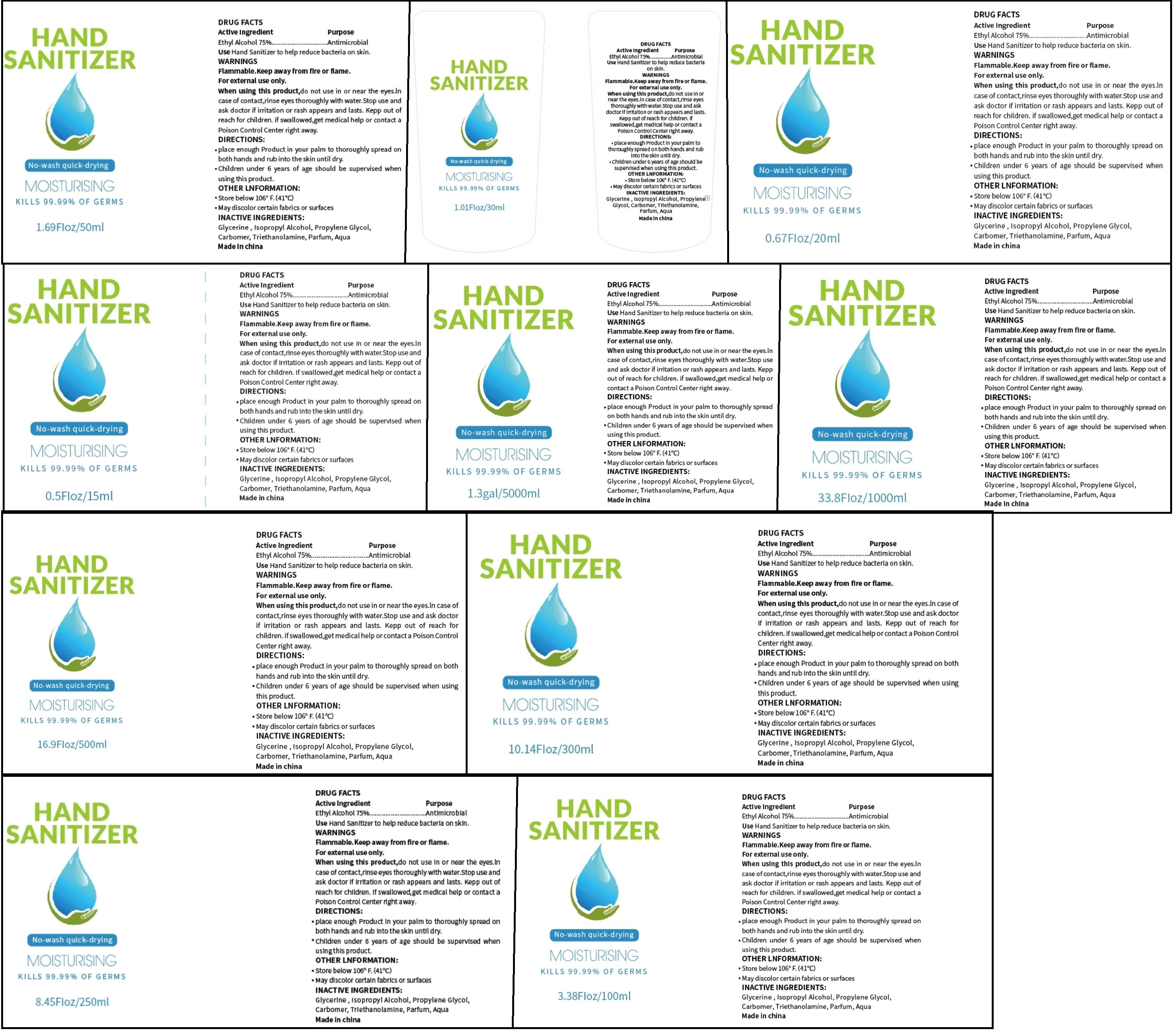 DRUG LABEL: HAND SANITIZER
NDC: 59541-541 | Form: GEL
Manufacturer: Huizhou Yiyani Cosmetic Co., Ltd.
Category: otc | Type: HUMAN OTC DRUG LABEL
Date: 20200722

ACTIVE INGREDIENTS: ALCOHOL 75 mL/100 mL
INACTIVE INGREDIENTS: PROPYLENE GLYCOL; CARBOMER HOMOPOLYMER, UNSPECIFIED TYPE; TROLAMINE; METHYL BENZOATE; GLYCERIN; ISOPROPYL ALCOHOL; WATER

HAND SANITIZER

Active Ingredient(s)

Ethyl Alcohol 75%

Purpose

Antimicrobial

Use

hand sanitizer to help reduce bacteria on skin

Warnings

Flammable. Keep away from fire or flame
Forexternal use only.

Do not use

/

When using this product, do not use in or near the eyes. In case of contact, rinse eyes thoroughly with water

Stop use and ask doctor if irritation or rash appears and lasts

KEEP OUT OF REACH OF CHILDREN

Kepp out of reach for children. if swallowed, get medical help or contact a Poison Control Center right away

Directions

place enough product in your palm to thoroughly spread on both hands and rub into the skin until dry
Children under 6 years of age should be supervised when using this product.

Other information

store below106°F(41°C)
May discolor certain fabrics or surfaces

Inactive ingredients

Glycerine, Isopropyl Alcohol, Propylene glycol, Carbomer, Triethanolamine, Parfum, aqua